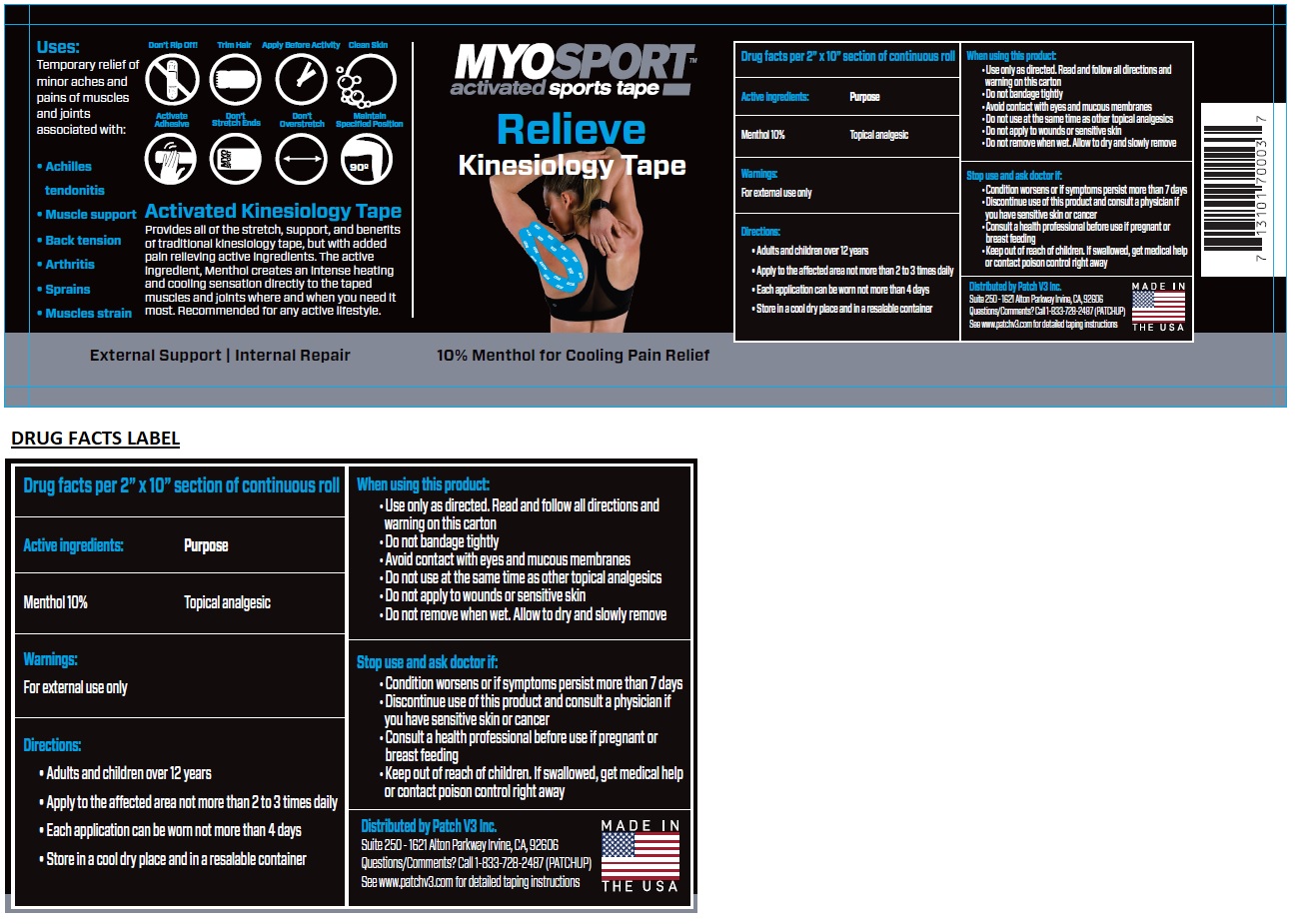 DRUG LABEL: MYOSPORT Relieve Kinesiology
NDC: 73729-845 | Form: TAPE
Manufacturer: Patchv3 Vitamins Ltd
Category: otc | Type: HUMAN OTC DRUG LABEL
Date: 20211108

ACTIVE INGREDIENTS: MENTHOL, UNSPECIFIED FORM 10 g/100 g
INACTIVE INGREDIENTS: METHACRYLIC ACID; 2-ETHYLHEXYL ACRYLATE; BENTONITE; SODIUM STEARATE; PPG-26 OLEATE

MYOSPORT Relieve Kinesiology Tape

Active ingredients:

Menthol 10%

Purpose

Topical analgesic

Uses:

Temporary relief of minor aches and pains of muscles and joints associated with:

• Achilles tendonitis

• Muscle support

• Back tension

• Arthritis

• Sprains

• Muscles strain

Warnings:

For external use only

When using this product:

• Use only as directed. Read and follow all directions and warning on this carton

• Do not bandage tightly

• Avoid contact with eyes and mucous membranes

• Do not use at the same time as other topical analgesics

• Do not apply to wounds or sensitive skin

• Do not remove when wet. Allow to dry and slowly remove

Stop use and ask doctor if:

• Condition worsens or if symptoms persist more than 7 days

• Discontinue use of this product and consult a physician if you have sensitive skin or cancer

• Consult a health professional before use if pregnant or breast feeding

• Keep out of reach of children. If swallowed, get medical help or contact poison control right away

Directions:

• Adults and children over 12 years

• Apply to the affected area not more than 2 to 3 times daily

• Each application can be worn not more than 4 days

• Store in a cool dry place and in a resalable container

Inactive ingredients:

Methacrylic acid, Ethylhexylacrylate, Bentonite, Sodium stearate, Polypropylene Glycol

activated sports tape

Activated Kinesiology Tape

Provides all of the stretch, support, and benefits of traditional kinesiology tape, but with added pain relieving active ingredients.

The active ingredient, Menthol creates an intense heating and cooling sensation directly to the taped muscles and joints where

and when you need it most. Recommended for any active lifestyle.

External Support | Internal Repair

10% Menthol for Cooling Pain Relief

Distributed by Patch V3 Inc.

Suite 250 - 1621 Alton Parkway Irvine, CA, 92606

Questions/Comments? Call 1-833-728-2487 (PATCHUP)

See www.patchv3.com for detailed taping instructions

MADE IN THE USA